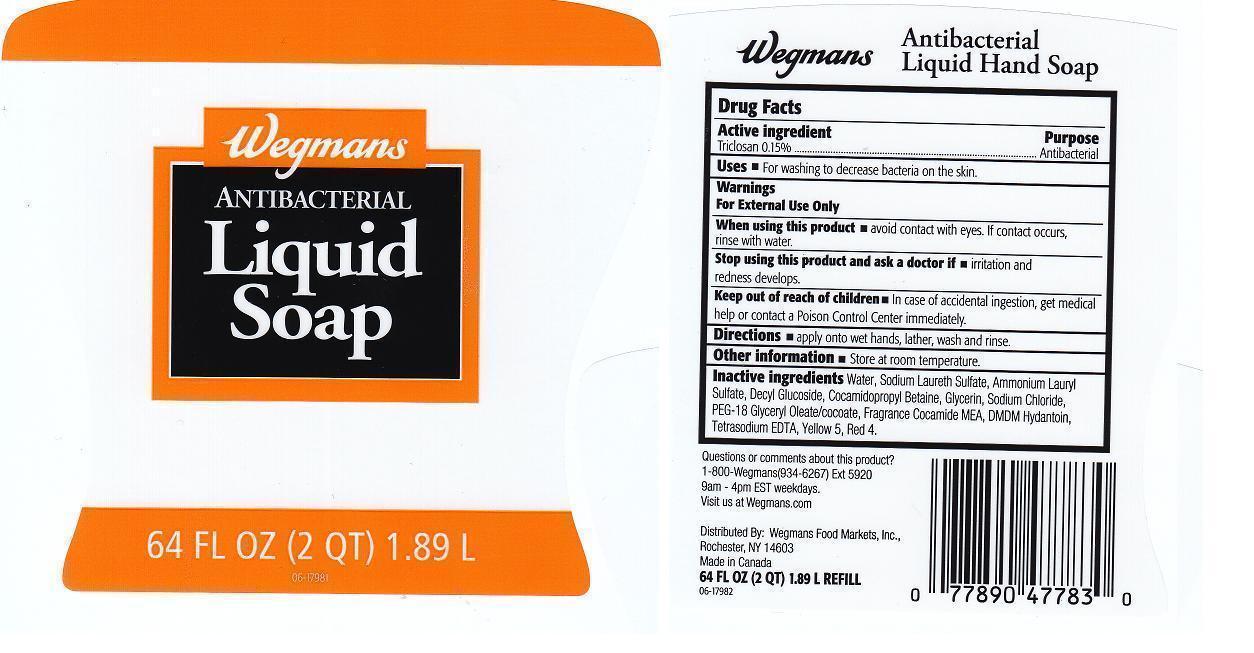 DRUG LABEL: WEGMANS
NDC: 47124-299 | Form: LIQUID
Manufacturer: WEGMANS FOOD MARKETS INC.
Category: otc | Type: HUMAN OTC DRUG LABEL
Date: 20130401

ACTIVE INGREDIENTS: TRICLOSAN 1.5 mg/1 mL
INACTIVE INGREDIENTS: WATER; SODIUM LAURETH SULFATE; AMMONIUM LAURYL SULFATE; DECYL GLUCOSIDE; COCAMIDOPROPYL BETAINE; GLYCERIN; SODIUM CHLORIDE; PEG-18 GLYCERYL OLEATE/COCOATE; COCO MONOETHANOLAMIDE; DMDM HYDANTOIN; EDETATE SODIUM; FD&C YELLOW NO. 5; FD&C RED NO. 4

DRUG FACTS

ACTIVE INGREDIENT

TRICLOSAN 0.15%

PURPOSE

ANTIBACTERIAL

USES

FOR WASHING TO DECREASE BACTERIA ON THE SKIN.

WARNNGS

FOR EXTERNAL USE ONLY.

WHEN USING THIS PRODUCT

AVOID CONTACT WITH EYES. IF CONTACT OCCURS, RINSE WITH WATER.

STOP USING THIS PRODUCT AND ASK A DOCTOR IF

IRRITATION AND REDNESS DEVELOPS.

KEEP OUT OF REACH OF CHILDREN

IN CASE OF ACCIDENTAL INGESTION, GET MEDICAL HELP OR CONTACT A POISON CONTROL CENTER IMMEDIATELY.

DIRECTIONS

APPLY ONTO WET HANDS, LATHER, WASH AND RINSE.

OTHER IFORMATION

STORE AT ROOM TEMPERATURE.

INACTIVE INGREDIENTS

WATER, SODIUM LAURETH SULFATE, AMMONIUM LAURYL SULFATE, DECYL GLUCOSIDE, COCAMIDOPROPYL BETAINE, GLYCERIN, SODIUM CHLORIDE, PEG-18 GLYCERYL OLEATE/COCOATE, FRAGRANCE, COCAMIDE MEA, DMDM HYDANTOIN, TETRASODIUM EDTA, YELLOW 5, RED 4.